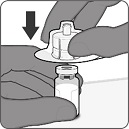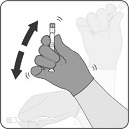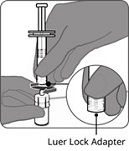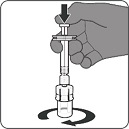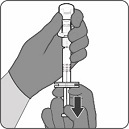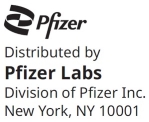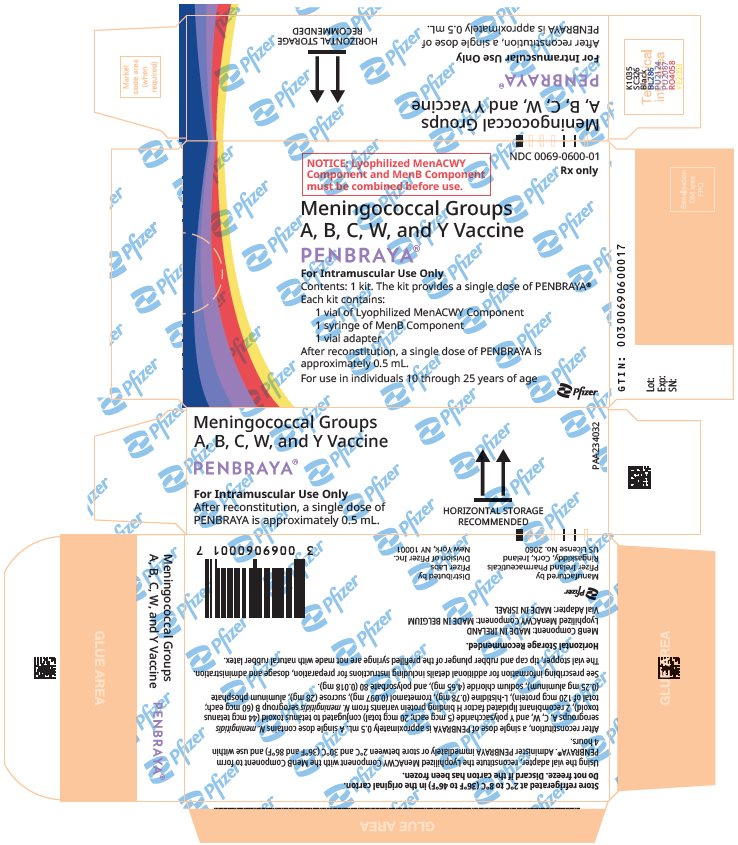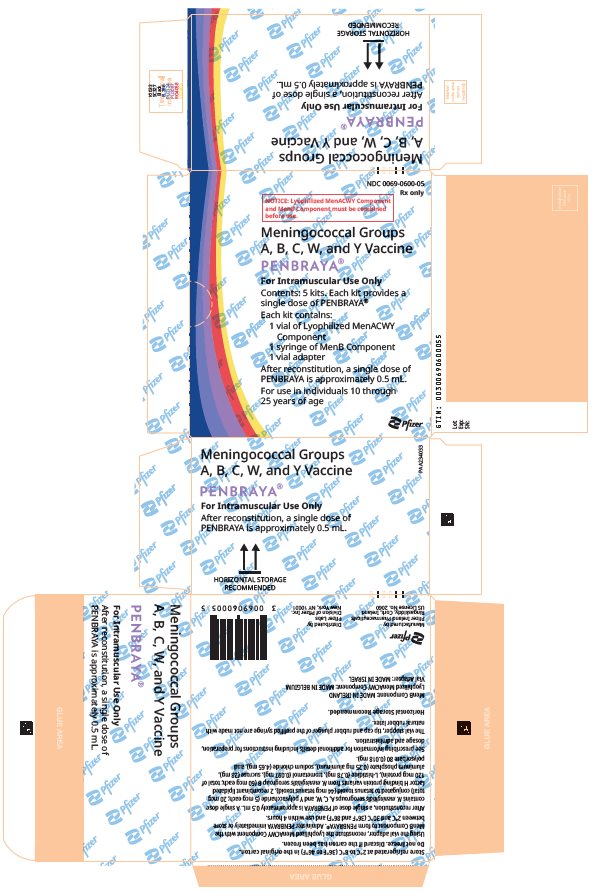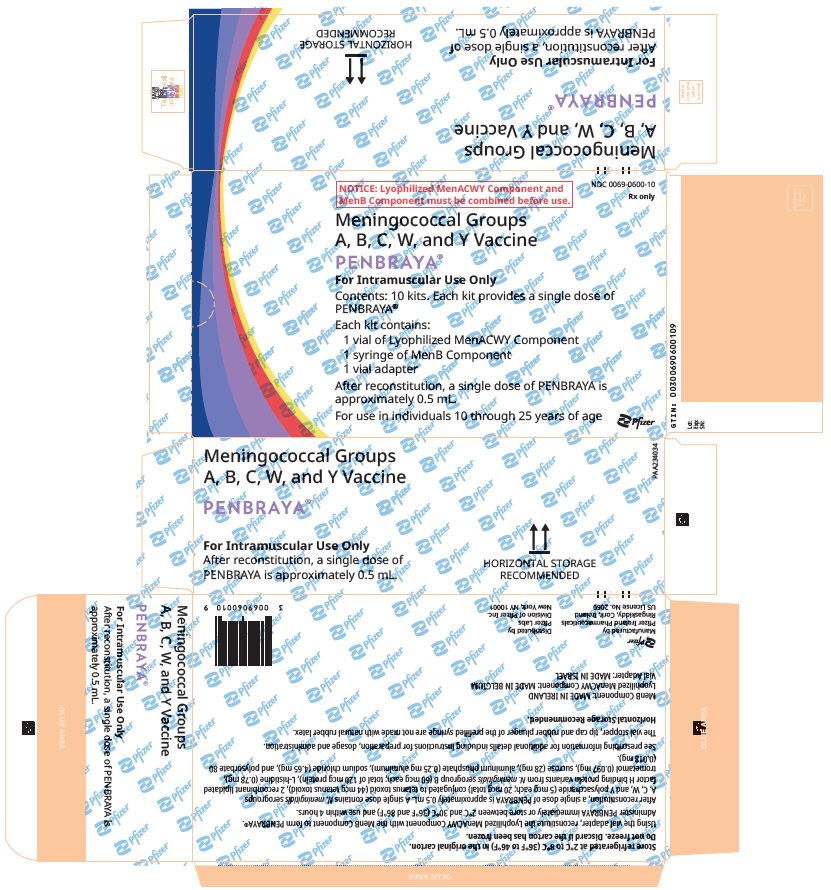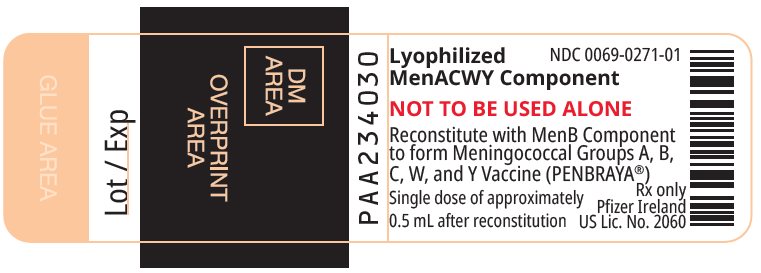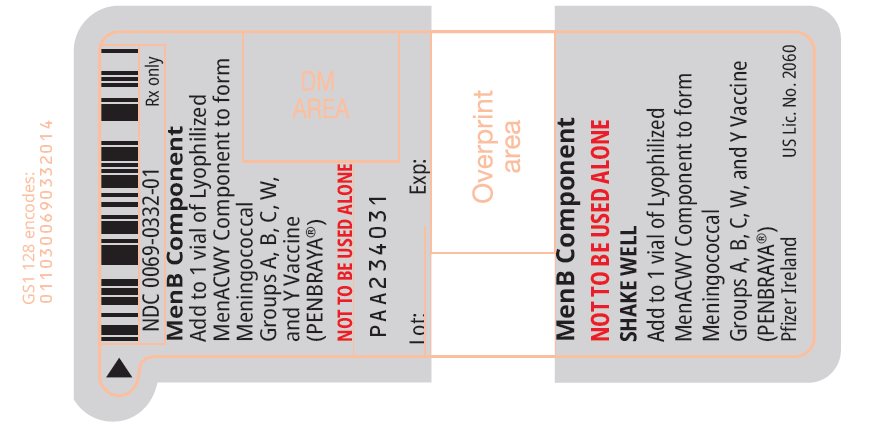 DRUG LABEL: PENBRAYA
NDC: 0069-0600 | Form: KIT | Route: INTRAMUSCULAR
Manufacturer: Pfizer Laboratories Div Pfizer Inc
Category: other | Type: VACCINE LABEL
Date: 20251124

ACTIVE INGREDIENTS: NEISSERIA MENINGITIDIS GROUP A CAPSULAR POLYSACCHARIDE TETANUS TOXOID CONJUGATE ANTIGEN 5 ug/0.5 mL; NEISSERIA MENINGITIDIS GROUP C CAPSULAR POLYSACCHARIDE TETANUS TOXOID CONJUGATE ANTIGEN 5 ug/0.5 mL; NEISSERIA MENINGITIDIS GROUP W-135 CAPSULAR POLYSACCHARIDE TETANUS TOXOID CONJUGATE ANTIGEN 5 ug/0.5 mL; NEISSERIA MENINGITIDIS GROUP Y CAPSULAR POLYSACCHARIDE TETANUS TOXOID CONJUGATE ANTIGEN 5 ug/0.5 mL; NEISSERIA MENINGITIDIS GROUP B RECOMBINANT LP2086 A05 PROTEIN VARIANT ANTIGEN 0.06 mg/0.5 mL; NEISSERIA MENINGITIDIS GROUP B RECOMBINANT LP2086 B01 PROTEIN VARIANT ANTIGEN 0.06 mg/0.5 mL
INACTIVE INGREDIENTS: CLOSTRIDIUM TETANI TOXOID ANTIGEN (FORMALDEHYDE INACTIVATED) 44 ug/0.5 mL; TROMETHAMINE 97 ug/0.5 mL; SUCROSE 28 mg/0.5 mL; SODIUM CHLORIDE 4.38 mg/0.5 mL; HISTIDINE 0.78 mg/0.5 mL; POLYSORBATE 80 0.018 mg/0.5 mL; ALUMINUM PHOSPHATE 0.25 mg/0.5 mL; WATER 498 mg/0.5 mL

HIGHLIGHTS OF PRESCRIBING INFORMATION

These highlights do not include all the information needed to use PENBRAYA safely and effectively. See full prescribing information for PENBRAYA.
PENBRAYA® (Meningococcal Groups A, B, C, W, and Y Vaccine), suspension for intramuscular injection
Initial U.S. Approval: 2023

1 INDICATIONS AND USAGE

PENBRAYA is indicated for active immunization to prevent invasive disease caused by Neisseria meningitidis serogroups A, B, C, W, and Y. PENBRAYA is approved for use in individuals 10 through 25 years of age. (1)

2 DOSAGE AND ADMINISTRATION

- For intramuscular use only. (2)
- Administer 2 doses (approximately 0.5 mL each) of PENBRAYA 6 months apart. (2.1)
- To prepare PENBRAYA, reconstitute the Lyophilized MenACWY Component with the MenB Component. (2.2)

3 DOSAGE FORMS AND STRENGTHS

PENBRAYA is a suspension for injection. A single dose after reconstitution is approximately 0.5 mL. (3)

4 CONTRAINDICATIONS

Severe allergic reaction (e.g., anaphylaxis) to any component of PENBRAYA. (4)

6 ADVERSE REACTIONS

The most commonly reported (≥15%) solicited adverse reactions after Dose 1 and Dose 2, respectively, were pain at the injection site (89% and 84%), fatigue (52% and 48%), headache (47% and 40%), muscle pain (26% and 23%), injection site redness (26% and 23%), injection site swelling (25% and 24%), joint pain (20% and 18%), and chills (20% and 16%). (6)

To report SUSPECTED ADVERSE REACTIONS, contact Pfizer Inc. at 1-800-438-1985 or VAERS at 1-800-822-7967 or http://vaers.hhs.gov.

FULL PRESCRIBING INFORMATION

1 INDICATIONS AND USAGE

PENBRAYA is indicated for active immunization to prevent invasive disease caused by Neisseria meningitidis serogroups A, B, C, W, and Y. PENBRAYA is approved for use in individuals 10 through 25 years of age.

2 DOSAGE AND ADMINISTRATION

For intramuscular use only.

2.1 Dose and Schedule

Administer 2 doses (approximately 0.5 mL each) of PENBRAYA 6 months apart.

2.2 Preparation

PENBRAYA is supplied in a kit that includes a vial of Lyophilized MenACWY Component (a sterile white powder), a prefilled syringe containing the MenB Component and a vial adapter.

To form PENBRAYA, reconstitute the Lyophilized MenACWY Component with the MenB Component as described in the instructions below.

Step 1. Attachment of the vial adapter to the vial.

- Remove the flip top cap from the vial of Lyophilized MenACWY Component.
- Peel off the top cover from the vial adapter packaging.
- While keeping the vial adapter in its packaging, center the adapter over the vial’s stopper and attach to the vial with a straight downward push.
- Remove the packaging.

Step 2. Resuspension of the MenB Component.

- Shake the syringe containing the MenB Component vigorously to obtain a white homogenous suspension. Do not use if the contents cannot be resuspended.

Step 3. Connection of the syringe containing the MenB Component to the vial adapter.

- Hold the syringe by the Luer lock adapter.
- Twist to remove the syringe cap.
- Connect the syringe to the vial adapter by turning the Luer lock.

Step 4. Reconstitution of the Lyophilized MenACWY Component with the MenB Component to form PENBRAYA.

- Inject the entire contents of the syringe into the vial.
- Hold the plunger rod down and gently swirl the vial until the powder is completely dissolved (less than 1 minute).

Step 5. Withdrawal of PENBRAYA.

- Invert the vial completely and slowly withdraw the entire contents into the syringe for an approximately 0.5 mL dose of PENBRAYA.
- Twist to disconnect the syringe from the vial adapter.
- Attach a sterile needle suitable for intramuscular injection.

2.3 Administration

For intramuscular use only.

After reconstitution, PENBRAYA is a homogeneous white suspension. If the vaccine is not a homogenous suspension, shake to resuspend prior to administration. Parenteral drug products should be inspected visually for particulate matter and discoloration prior to administration, whenever solution and container permit. Discard if either condition is present.

Administer PENBRAYA immediately or store between 2°C and 30°C (36°F and 86°F) and use within 4 hours. Discard reconstituted vaccine if not used within 4 hours.

3 DOSAGE FORMS AND STRENGTHS

PENBRAYA is a suspension for injection.

A single dose after reconstitution is approximately 0.5 mL.

4 CONTRAINDICATIONS

Do not administer PENBRAYA to individuals with a history of severe allergic reaction (e.g., anaphylaxis) to any component of PENBRAYA [see Description (11)].

5 WARNINGS AND PRECAUTIONS

5.1 Management of Acute Allergic Reactions

Appropriate medical treatment used to manage immediate allergic reactions must be immediately available in the event an anaphylactic reaction occurs following administration of PENBRAYA.

5.2 Syncope

Syncope (fainting) may occur in association with administration of injectable vaccines, including PENBRAYA. Procedures should be in place to avoid injury from fainting.

5.3 Altered Immunocompetence

Reduced Immune Response

Some individuals with altered immunocompetence may have reduced immune responses to PENBRAYA.

Complement Deficiency

Individuals with certain complement deficiencies and individuals receiving treatment that inhibits terminal complement activation are at increased risk for invasive disease caused by N. meningitidis groups A, B, C, W, and Y, even if they develop antibodies following vaccination with PENBRAYA [see Clinical Pharmacology (12.1)].

5.4 Limitations of Vaccine Effectiveness

Vaccination with PENBRAYA may not protect all vaccine recipients.

5.5 Tetanus Immunization

Vaccination with PENBRAYA does not substitute for vaccination with a tetanus toxoid containing vaccine to prevent tetanus.

5.6 Guillain-Barré Syndrome

Guillain-Barré syndrome (GBS) has been reported in temporal relationship following administration of another U.S.-licensed meningococcal quadrivalent polysaccharide conjugate vaccine. The decision by the healthcare professional to administer PENBRAYA to persons with a history of GBS should take into account the expected benefits and potential risks.

6 ADVERSE REACTIONS

The most commonly reported (≥15%) solicited adverse reactions after Dose 1 and Dose 2, respectively, were pain at the injection site (89% and 84%), fatigue (52% and 48%), headache (47% and 40%), muscle pain (26% and 23%), injection site redness (26% and 23%), injection site swelling (25% and 24%), joint pain (20% and 18%), and chills (20% and 16%).

6.1 Clinical Trials Experience

Because clinical trials are conducted under widely varying conditions, adverse reaction rates observed in the clinical trials of a vaccine cannot be directly compared to rates in the clinical trials of another vaccine and may not reflect the rates observed in practice.

The safety of PENBRAYA in individuals 10 through 25 years of age was evaluated in 3 clinical studies (2 active-controlled and 1 non-controlled study). In the controlled studies, 2306 participants received at least 1 dose of PENBRAYA. Of 946 participants who had previously received a meningococcal conjugate vaccine (categorized as MenACWY conjugate vaccine-exposed), 802 participants had received 1 dose of any U.S.-licensed Meningococcal Groups A, C, W, and Y conjugate vaccine, 51 participants had received a non-U.S.-licensed monovalent Meningococcal Group C conjugate vaccine (MenC conjugate vaccine), and 93 participants had received an unspecified U.S.-licensed or non-U.S.-licensed MenACWY conjugate or a MenC conjugate vaccine at least 4 years prior to enrollment. In the non-controlled study, 300 participants received a single dose of PENBRAYA.

Study 1 (NCT04440163) was an active-controlled, observer-blinded, multicenter study in which participants 10 through 25 years of age in the U.S. and Europe received at least 1 dose of PENBRAYA (N=1763) or Meningococcal Group B Vaccine (Trumenba) (N=650) at 0 and 6 months. Meningococcal Groups A, C, Y, and W-135 Oligosaccharide Diphtheria CRM197 Conjugate Vaccine (MenACWY-CRM, GSK Vaccines, SRL) was concomitantly administered with Trumenba at Month 0. All participants were MenB vaccine-naïve. Both MenACWY conjugate vaccine-naïve and MenACWY conjugate vaccine-exposed participants were part of the study.

Study 2 (NCT03135834) was an active-controlled, observer-blinded, multicenter study in which participants 10 through 25 years of age in the U.S. and Europe received at least 1 dose of PENBRAYA (N=543) or Trumenba (N=1057) at 0 and 6 months. MenACWY-CRM was co-administered with Trumenba at Month 0. All participants were MenB vaccine-naïve. Both MenACWY conjugate vaccine-naïve and MenACWY conjugate vaccine-exposed participants were part of this study.

Study 3 (NCT04440176) was a descriptive non-controlled study in which participants 11 through 14 years of age in the U.S. received PENBRAYA 12 months apart. All participants were naïve to any meningococcal vaccine.

In Study 1 and Study 2, solicited local and systemic adverse reactions were monitored for 7 days after study vaccination using an electronic diary. In all studies, spontaneous reports of adverse events (AEs) were collected through at least 1 month after the last vaccination, and through 6 months after the last vaccination for serious adverse events (SAEs).

In controlled studies, demographic characteristics were generally similar with regard to gender, race, and ethnicity among participants who received PENBRAYA and those who received control (Trumenba and MenACWY-CRM). Among participants who received PENBRAYA in controlled studies, 47.4% were male, 79.4% were White, 10.2% were Black or African-American, 2.1% were Asian, and 2.6% were of other racial groups, and 21.6% were of Hispanic/Latino ethnicity.

Solicited Local and Systemic Adverse Reactions

Table 1 presents the solicited local adverse reactions and Table 2 presents the solicited systemic adverse reactions and use of antipyretic medication reported within 7 days following each dose of PENBRAYA in Study 1.

Table 1. Percentage of Participants Reporting Solicited Local Adverse Reactions Within 7 Days After PENBRAYA or Trumenba Vaccination in Study 1 [NCT04440163]
Injection Site Reactions | PENBRAYA |  | Trumenba + MenACWY-CRM [Trumenba and MenACWY-CRM were administered at 0 month followed by Trumenba alone at 6 months. Local reactions were recorded only for PENBRAYA and Trumenba injection sites.]
Injection Site Reactions | Dose 1 | Dose 2 | Dose 1 | Dose 2
Injection Site Reactions | N=1724-1725; % | N=1456; % | N=630-631; % | N=529; %
Pain [Mild (does not interfere with activity); Moderate (interferes with activity); Severe (prevents daily activity).]
Any ["Any" is defined as the cumulative frequency of participants who reported a reaction as "mild", "moderate", or "severe" within 7 days of vaccination.] | 89.3 | 84.4 | 85.1 | 78.6
Mild | 32.3 | 29.1 | 31.1 | 33.1
Moderate | 49.4 | 48.8 | 47.7 | 40.3
Severe | 7.5 | 6.5 | 6.3 | 5.3
Redness [Mild (2.0 to 5 cm); Moderate (>5 to 10 cm); Severe (>10 cm).]
Any | 25.9 | 23.2 | 19.5 | 14.7
Mild | 8.9 | 7.7 | 7.3 | 6.6
Moderate | 14.4 | 12.6 | 10.0 | 7.2
Severe | 2.6 | 3.0 | 2.2 | 0.9
Swelling
Any | 25.0 | 24.2 | 21.4 | 14.7
Mild | 10.6 | 10.4 | 8.3 | 6.4
Moderate | 13.3 | 12.8 | 12.4 | 8.1
Severe | 1.2 | 1.0 | 0.8 | 0.2
Abbreviations: N = number of participants; MenACWY-CRM = meningococcal (serogroups A, C, W and Y) oligosaccharide diphtheria CRM197 conjugate vaccine; Trumenba = meningococcal serogroup B factor H binding protein.

Table 2. Percentage of Participants Reporting Solicited Systemic Adverse Reactions and Use of Antipyretic Medications Within 7 Days After Each Vaccination in Study 1
Systemic Reactions | PENBRAYA |  | Trumenba + MenACWY-CRM [Trumenba and MenACWY-CRM were administered at 0 month followed by Trumenba alone at 6 months.]
Systemic Reactions | Dose 1 | Dose 2 | Dose 1 | Dose 2
Systemic Reactions | N=1739-1740; % | N=1459; % | N=638; % | N=532; %
Fever (≥38°C)
≥38.0°C | 5.9 | 2.4 | 5.8 | 1.5
38.0° to 38.4°C | 3.7 | 1.9 | 2.0 | 0.4
>38.4° to 38.9°C | 1.6 | 0.3 | 2.8 | 0.9
>38.9° to 40.0°C | 0.6 | 0.2 | 0.9 | 0.2
>40.0°C | 0.0 | 0.0 | 0.0 | 0.0
Vomiting [Mild (1 to 2 times in 24 hours); Moderate (>2 times in 24 hours); Severe (requires intravenous hydration).]
Any ["Any" is defined as the cumulative frequency of participants who reported a reaction as "mild", "moderate", or "severe" within 7 days of vaccination.] | 3.2 | 1.5 | 3.0 | 0.9
Mild | 2.5 | 1.4 | 2.0 | 0.8
Moderate | 0.6 | 0.1 | 0.9 | 0.2
Severe | 0.0 | 0.0 | 0.0 | 0.0
Diarrhea [Mild (2 to 3 loose stools in 24 hours); Moderate (4 to 5 loose stools in 24 hours); Severe (6 or more loose stools in 24 hours).]
Any | 11.0 | 8.2 | 13.5 | 8.5
Mild | 8.7 | 6.9 | 11.9 | 6.0
Moderate | 2.0 | 1.4 | 1.6 | 2.4
Severe | 0.3 | 0.0 | 0.0 | 0.0
Headache [Mild (does not interfere with activity); Moderate (interferes with activity); Severe (prevents daily activity).]
Any | 46.8 | 39.8 | 46.9 | 37.8
Mild | 25.7 | 21.3 | 24.5 | 21.1
Moderate | 19.2 | 16.8 | 20.4 | 16.2
Severe | 1.9 | 1.7 | 2.0 | 0.6
Fatigue
Any | 52.1 | 47.6 | 54.7 | 43.6
Mild | 23.5 | 22.8 | 25.7 | 22.0
Moderate | 25.5 | 21.8 | 25.7 | 19.9
Severe | 3.2 | 2.9 | 3.3 | 1.7
Chills
Any | 20.1 | 16.4 | 19.6 | 16.2
Mild | 12.6 | 9.9 | 10.2 | 8.8
Moderate | 6.7 | 6.0 | 7.8 | 5.8
Severe | 0.8 | 0.4 | 1.6 | 1.5
Muscle pain (other than muscle pain at the injection site)
Any | 25.7 | 22.8 | 27.4 | 22.2
Mild | 13.6 | 10.0 | 13.5 | 10.0
Moderate | 10.5 | 11.9 | 11.9 | 11.5
Severe | 1.6 | 0.8 | 2.0 | 0.8
Joint pain
Any | 20.2 | 18.3 | 22.6 | 15.6
Mild | 10.7 | 9.6 | 12.9 | 7.9
Moderate | 8.6 | 8.3 | 8.6 | 6.8
Severe | 1.0 | 0.4 | 1.1 | 0.9
Use of antipyretic medication | 29.5 | 25.1 | 28.1 | 20.5
Abbreviations: N = number of participants; MenACWY-CRM = meningococcal (serogroups A, C, W and Y) oligosaccharide diphtheria CRM197 conjugate vaccine; Trumenba= meningococcal serogroup B factor H binding protein.

Serious Adverse Events

In Study 1, during the 30 days after vaccination visit 1 (at 0 months), <0.1% (1/1763) of PENBRAYA and 0% (0/649) of Trumenba + MenACWY-CRM participants reported at least 1 SAE. During the 30 days after vaccination visit 2 (at 6 months), 0.1% (2/1558) of PENBRAYA and 0% (0/562) of Trumenba participants reported at least 1 SAE. None of the SAEs were determined to be related to PENBRAYA vaccination.

In Study 2, during the 30 days after vaccination visit 1 (at 0 months), 0.4% (2/543) of PENBRAYA and 0% (0/1057) of Trumenba + MenACWY-CRM participants reported at least 1 SAE. During the 30 days after vaccination visit 2 (at 6 months), 0.2% (1/486) of PENBRAYA and 0% (0/946) of Trumenba participants reported at least 1 SAE. None of the SAEs were determined to be related to PENBRAYA vaccination.

In non-controlled Study 3, no SAEs (0/294) were reported within 30 days after either vaccination (0, 12 months).

6.2 Postmarketing Experience

The postmarketing safety experience with Trumenba and a non-U.S.-licensed Meningococcal Groups A, C, W, and Y polysaccharide tetanus toxoid (TT) conjugate vaccine (MenACWY-TT vaccine; Pfizer Inc.) is relevant to PENBRAYA since PENBRAYA includes the same group A, C, W, and Y TT-conjugated polysaccharide components and MenB recombinant protein components. Because these events are reported voluntarily from a population of uncertain size, it is not possible to reliably estimate their frequency or establish a causal relationship to vaccination. The following adverse reactions have been spontaneously reported during postmarketing use of Trumenba and MenACWY-TT and may also be seen in postmarketing experience with PENBRAYA.

Immune System Disorders: allergic reactions, including anaphylaxis

Nervous System: syncope (fainting)

8 USE IN SPECIFIC POPULATIONS

8.1 Pregnancy

Pregnancy Exposure Registry

There is a pregnancy exposure registry that monitors pregnancy outcomes in individuals exposed to PENBRAYA during pregnancy. Individuals who received PENBRAYA during pregnancy are encouraged to contact, or have their healthcare provider contact, 1-877-390-2953 to enroll in or obtain information about the registry.

Risk Summary

All pregnancies have a risk of birth defect, loss, or other adverse outcomes. In the U.S. general population, the estimated background risk of major birth defects and miscarriage in clinically recognized pregnancies is 2% to 4% and 15% to 20%, respectively.

There are no clinical studies of PENBRAYA in pregnant individuals. Available human data on PENBRAYA administered to pregnant individuals are insufficient to inform vaccine-associated risks in pregnancy.

There were no developmental toxicity studies performed with PENBRAYA.

8.2 Lactation

Risk Summary

There are no data available to assess the effects of PENBRAYA on the breastfed infant or on milk production/excretion. The developmental and health benefits of breastfeeding should be considered along with the mother's clinical need for PENBRAYA and any potential adverse effects on the breastfed child from PENBRAYA or from the underlying maternal condition. For preventive vaccines, the underlying maternal condition is susceptibility to disease prevented by the vaccine.

8.4 Pediatric Use

The safety and effectiveness of PENBRAYA have not been established in individuals <10 years of age. In a clinical study, 90% of infants younger than 12 months of age who were vaccinated with a reduced dosage formulation of Trumenba had fever. PENBRAYA contains the same MenB component, in the same quantity, as Trumenba.

8.5 Geriatric Use

The safety and effectiveness of PENBRAYA have not been established in individuals >65 years of age.

11 DESCRIPTION

PENBRAYA (Meningococcal Groups A, B, C, W, and Y Vaccine) is a suspension for intramuscular injection. PENBRAYA is supplied as a sterile Lyophilized MenACWY Component to be reconstituted with the sterile MenB Component.

The Lyophilized MenACWY Component consists of N. meningitidis serogroups A, C, W, and Y polysaccharides individually conjugated to TT. The polysaccharide for each group is grown in media containing dextrose, salt, and yeast extract, then purified by precipitation and filtration. The TT is produced by fermentation of Clostridium tetani in dextrose, salts, and tryptone N1 peptone followed by formalin detoxification, then purified by a series of physicochemical steps. The serogroups A and C polysaccharides are individually microfluidized, activated with 1-cyano-4(dimethylamino)-pyridinium tetrafluoroborate (CDAP), derivatized with adipic acid dihydrazide (ADH), and then conjugated with TT in the presence of 1-ethyl-3-(3-dimethylaminopropyl)carbodiimide) (EDAC). The serogroups W and Y polysaccharides are individually microfluidized, activated with CDAP, and then conjugated with TT. The conjugates are purified by a series of physicochemical steps then sterile filtered. Trometamol/sucrose buffer is added, and the MenACWY-TT solution is lyophilized.

The MenB Component is a sterile suspension composed of 2 recombinant lipidated factor H binding protein (fHbp) variants from N. meningitidis serogroup B, 1 from fHbp subfamily A and 1 from fHbp subfamily B (A05 and B01, respectively). The proteins are individually produced in Escherichia coli. Production strains are grown to a specific density in chemically defined fermentation growth media without antibiotics or animal-derived components. The recombinant proteins are extracted from the production strains and purified through a series of column chromatography steps. Polysorbate 80 (PS80) is added and is present in the MenB Component.

Each approximately 0.5 mL dose of PENBRAYA contains N. meningitidis serogroup A, C, W, and Y polysaccharide (5 mcg each; 20 mcg total) conjugated to tetanus toxoid (44 mcg tetanus toxoid), 2 recombinant lipidated factor H binding protein variants from N. meningitidis serogroup B (60 mcg each; total of 120 mcg protein), L-histidine (0.78 mg) , trometamol (0.097 mg), sucrose (28 mg), aluminum phosphate (0.25 mg aluminum), sodium chloride (4.65 mg), and PS80 80 (0.018 mg) at pH 6.0.

PENBRAYA does not contain any preservatives.

12 CLINICAL PHARMACOLOGY

12.1 Mechanism of Action

Protection against invasive meningococcal disease is conferred mainly by complement-mediated antibody-dependent killing of N. meningitidis.^1 Vaccination with PENBRAYA induces the production of bactericidal antibodies specific to the capsular polysaccharides of N. meningitidis serogroups A, C, W, and Y and to fHbp subfamily A and B variants of N. meningitidis group B. The susceptibility of group B meningococci to bactericidal antibody is dependent upon both the antigenic similarity of the fHbp subfamily A or subfamily B vaccine antigen to the fHbp protein expressed by the bacterial strain and the amount of fHbp expressed at the bacterial surface.^2

13 NONCLINICAL TOXICOLOGY

13.1 Carcinogenesis, Mutagenesis, Impairment of Fertility

PENBRAYA has not been evaluated for the potential to cause carcinogenicity, genotoxicity, or impairment of fertility.

14 CLINICAL STUDIES

The effectiveness of PENBRAYA was assessed in Study 1 by measuring antibodies with assays that used human complement to assess serum bactericidal activity (hSBA). For serogroups A, C, W, and Y, one strain was utilized per group. For serogroup B, four meningococcal serogroup B strains expressing different fHbp variants that represent the A and B subfamilies of meningococcal serogroup B strains causing invasive disease in the U.S. and Europe were utilized. The proportions of subjects with a 4-fold or greater increase in hSBA titer for each strain, and the proportion of subjects with a titer greater than or equal to the lower limit of quantitation (LLOQ) of the assay for all four serogroup B strains (composite response) were assessed.

14.1 Immunogenicity

Study 1 was a Phase 3, randomized, active-controlled, observer-blinded, multicenter study in which participants 10 through 25 years of age in the U.S. and Europe received PENBRAYA at 0 and 6 months or Trumenba at 0 and 6 months and MenACWY-CRM at 0 months. All participants were MenB vaccine-naïve. Both MenACWY conjugate vaccine -naïve and MenACWY conjugate vaccine-exposed participants were part of the study.

Seroresponse for serogroups A, B, C, W, and Y and composite response for serogroup B following 2 doses of PENBRAYA in Study 1 are presented in Tables 3 and 4.

Among both ACWY-naïve and ACWY-exposed participants, seroresponse rates to serogroups A, C, W, and Y following 2 doses of PENBRAYA were demonstrated to be non-inferior to seroresponse rates following a single dose of MenACWY-CRM. Seroresponse and composite response rates to serogroup B primary strains among participants who received 2 doses of PENBRAYA were demonstrated to be non-inferior to seroresponse and composite response rates following 2 doses of Trumenba.

Table 3. Percentage of Subjects Achieving Seroresponses 1 Month after Receiving 2 Doses of PENBRAYA (0 and 6 Months) versus 1 Month after Single Dose of MenACWY-CRM for Serogroups A, C, W, and Y (Study 1) [Evaluable immunogenicity populations.] , [NCT04440163]
Serogroup | PENBRAYA; % | Trumenba + MenACWY-CRM; % | PENBRAYA – MenACWY-CRM; Difference [Non-inferiority was demonstrated (using 10% margin) post-vaccination by assessing the difference between vaccination serogroups.]
Serogroup | N=439-451 (Naïve); N=376-387 (Exposed) | N=244-254 (Naïve); N=222-227 (Exposed) | Difference %; (95% CI)
A
ACWY-naïve | 97.8 | 95.3 | 2.5; (-0.2, 6.0)
ACWY-exposed | 93.8 | 96.9 | -3.2; (-6.5, 0.5)
C
ACWY-naïve | 93.3 | 52.4 | 41.0; (34.4, 47.5)
ACWY-exposed | 93.8 | 94.7 | -0.9; (-4.6, 3.3)
W
ACWY- naïve | 97.3 | 73.0 | 24.3; (18.8, 30.4)
ACWY-exposed | 97.1 | 96.4 | 0.7; (-2.2, 4.3)
Y
ACWY- naïve | 94.4 | 70.6 | 23.8; (18.0, 30.1)
ACWY-exposed | 93.0 | 93.7 | -0.7; (-4.6, 3.8)
Abbreviations: CI = confidence interval; hSBA = serum bactericidal assay using human complement; LLOQ = lower limit of quantitation; LOD = limit of detection; MenACWY-CRM = meningococcal (serogroups A, C, W and Y) oligosaccharide diphtheria CRM197 conjugate vaccine; Trumenba= meningococcal serogroup B factor H binding protein.
Note: The LLOQ is an hSBA titer = 1:16 for A22 and 1:8 for A56, B24, and B44 and serogroups A, C, W, and Y.
Note: Seroresponse is defined as the 4-fold increase as follows: (1) For participants with a baseline hSBA titer <1:4 (LOD), a 4-fold response was defined as an hSBA titer ≥1:16. (2) For participants with a baseline hSBA titer ≥ LOD and < LLOQ, a response is defined as an hSBA titer ≥4 times the LLOQ. (3) For participants with a baseline hSBA titer ≥ LLOQ, a response is defined as an hSBA titer ≥4 times the baseline titer.

Table 4. Percentage of Participants Achieving Seroresponses and Composite Response 1 Month after Receiving 2 Doses of PENBRAYA (0 and 6 Months) versus 2 Doses of Trumenba (0 and 6 Months) For Serogroup B (Study 1) [Evaluable immunogenicity populations.] , [NCT04440163]
 | PENBRAYA; % | Trumenba + MenACWY-CRM; % | PENBRAYA – Trumenba; Difference
Serogroup B Variant | N=755-845 | N=383-419 | Difference %; (95% CI)
Seroresponse [Non-inferiority was demonstrated (using 10% margin) post-vaccination by assessing the difference between vaccination serogroups.]
A22 | 83.0 | 79.0 | 4.0; (-0.7, 8.9)
A56 | 95.9 | 94.5 | 1.4; (-1.0, 4.3)
B24 | 68.1 | 57.2 | 10.9; (5.2, 16.6)
B44 | 86.5 | 79.2 | 7.3; (2.9, 11.9)
Composite [Composite response = hSBA ≥ LLOQ for all 4 primary meningococcal B strains.]
Pre-Dose 1 | 1.2 | 2.0 | -
Post-Dose 2 | 78.3 | 68.7 | 9.6; (4.2, 15.2)
Abbreviations: CI = confidence interval; hSBA = serum bactericidal assay using human complement; LLOQ = lower limit of quantitation; LOD = limit of detection; MenACWY-CRM = meningococcal (serogroups A, C, W and Y) oligosaccharide diphtheria CRM197 conjugate vaccine; Trumenba= meningococcal serogroup B factor H binding protein.
Note: The LLOQ is an hSBA titer = 1:16 for A22 and 1:8 for A56, B24, and B44 and serogroups A, C, W, and Y.
Note: Seroresponse is defined as the 4-fold increase as follows: (1) For participants with a baseline hSBA titer <1:4 (LOD), a 4-fold response was defined as an hSBA titer ≥1:16. (2) For participants with a baseline hSBA titer ≥ LOD and < LLOQ, a response is defined as an hSBA titer ≥4 times the LLOQ. (3) For participants with a baseline hSBA titer ≥ LLOQ, a response is defined as an hSBA titer ≥4 times the baseline titer.

15 REFERENCES

1. Goldschneider I, Gotschlich EC, Artenstein MS. Human immunity to the meningococcus. I. The role of humoral antibodies. J Exp Med. (1969);129:1307–1326.
2. Wang X, et al. Prevalence and genetic diversity of candidate vaccine antigens among invasive Neisseria meningitidis isolates in the U.S. Vaccine 2011; 29:4739-4744.

16 HOW SUPPLIED/STORAGE AND HANDLING

16.1 How Supplied

PENBRAYA is supplied in a kit that includes a vial of Lyophilized MenACWY Component (NDC 0069-0271-01), a prefilled syringe containing MenB Component (NDC 0069-0332-01) and a vial adapter. The Lyophilized MenACWY Component is reconstituted with the MenB Component to form a single dose of PENBRAYA.

PENBRAYA is supplied in cartons of 1, 5, and 10 kits.

Carton: 1 kit | 0069-0600-01
Carton: 5 kits | 0069-0600-05
Carton: 10 kits | 0069-0600-10

The vial stopper and the syringe tip cap and plunger stopper are not made with natural rubber latex.

16.2 Storage Before Reconstitution

Store refrigerated at 2°C to 8°C (36°F to 46°F) in the original carton. During storage, a white deposit and clear supernatant may be observed in the prefilled syringe containing the MenB Component. Store the carton horizontally to minimize the time necessary to resuspend the MenB Component.

Do not freeze. Discard if the carton has been frozen.

16.3 Storage After Reconstitution

After reconstitution, administer PENBRAYA immediately or store between 2°C and 30°C (36°F and 86°F) and use within 4 hours. Do not freeze.

17 PATIENT COUNSELING INFORMATION

Prior to administration of PENBRAYA:

- Inform vaccine recipient of the potential benefits and risks of vaccination with PENBRAYA.
- Advise vaccine recipient to report any adverse events to their healthcare provider or to the Vaccine Adverse Event Reporting System at 1-800-822-7967 and https://vaers.hhs.gov/.

This product’s labeling may have been updated. For the most recent prescribing information, please visit https://dailymed.nlm.nih.gov/dailymed/.

Manufactured by:
Pfizer Ireland Pharmaceuticals
Ringaskiddy, Cork, Ireland

US License No. 2060

LAB-1512-4.0

PRINCIPAL DISPLAY PANEL - 1 Vial/Syringe Kit Carton

NDC 0069-0600-01
Rx only

NOTICE: Lyophilized MenACWY
Component and MenB Component
must be combined before use.

Meningococcal Groups
A, B, C, W, and Y Vaccine
PENBRAYA®

For Intramuscular Use Only
Contents: 1 kit. The kit provides a single dose of PENBRAYA®
Each kit contains:
1 vial of Lyophilized MenACWY Component
1 syringe of MenB Component
1 vial adapter

After reconstitution, a single dose of PENBRAYA is
approximately 0.5 mL.

For use in individuals 10 through 25 years of age

Pfizer

PRINCIPAL DISPLAY PANEL - 5 Vial/Syringe Kit Carton

NDC 0069-0600-05
Rx only

NOTICE: Lyophilized MenACWY Component
and MenB Component must be combined
before use.

Meningococcal Groups
A, B, C, W, and Y Vaccine
PENBRAYA®

For Intramuscular Use Only
Contents: 5 kits. Each kit provides a
single dose of PENBRAYA®
Each kit contains:
1 vial of Lyophilized MenACWY
Component
1 syringe of MenB Component
1 vial adapter

After reconstitution, a single dose of
PENBRAYA is approximately 0.5 mL.

For use in individuals 10 through
25 years of age

Pfizer

PRINCIPAL DISPLAY PANEL - 10 Vial/Syringe Kit Carton

NDC 0069-0600-10
Rx only

NOTICE: Lyophilized MenACWY Component and
MenB Component must be combined before use.

Meningococcal Groups
A, B, C, W, and Y Vaccine
PENBRAYA®

For Intramuscular Use Only
Contents: 10 kits. Each kit provides a single dose of
PENBRAYA®
Each kit contains:
1 vial of Lyophilized MenACWY Component
1 syringe of MenB Component
1 vial adapter

After reconstitution, a single dose of PENBRAYA is
approximately 0.5 mL.

For use in individuals 10 through 25 years of age

Pfizer

PRINCIPAL DISPLAY PANEL - 1 Vial Label

Lyophilized
MenACWY Component

NDC 0069-0271-01

NOT TO BE USED ALONE

Reconstitute with MenB Component
to form Meningococcal Groups A, B,
C, W, and Y Vaccine (PENBRAYA®)

Single dose of approximately
0.5 mL after reconstitution

Rx only
Pfizer Ireland
US Lic. No. 2060

PRINCIPAL DISPLAY PANEL - 1 Syringe Label

NDC 0069-0332-01
Rx only

MenB Component
Add to 1 vial of Lyophilized
MenACWY Component to form
Meningococcal
Groups A, B, C, W,
and Y Vaccine
(PENBRAYA®)

NOT TO BE USED ALONE

PAA234031

Lot:
Exp:

MenB Component

NOT TO BE USED ALONE

SHAKE WELL

Add to 1 vial of Lyophilized
MenACWY Component to form
Meningococcal
Groups A, B, C, W, and Y Vaccine
(PENBRAYA®)

Pfizer Ireland
US Lic. No. 2060